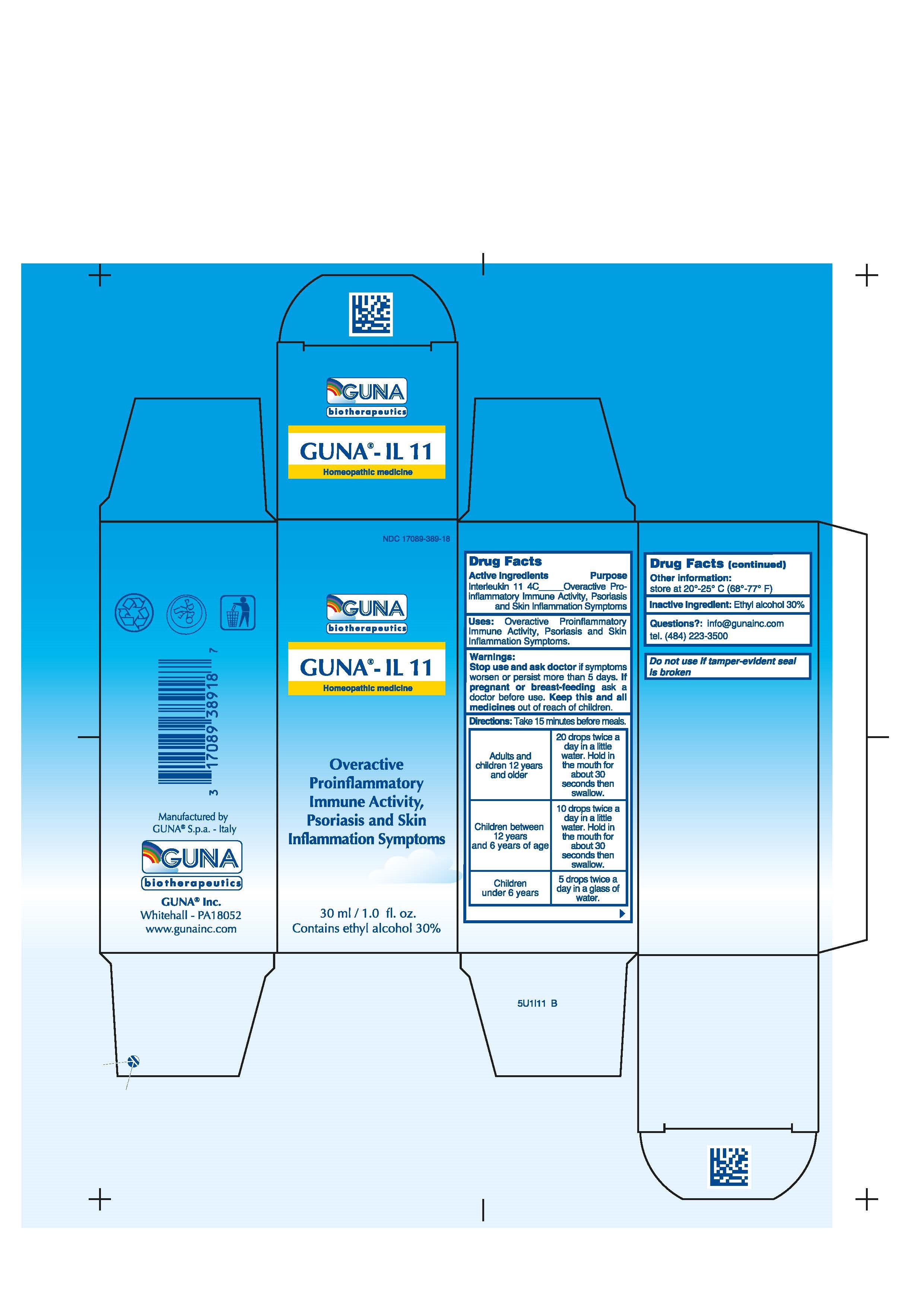 DRUG LABEL: GUNA-IL 11
NDC: 17089-389 | Form: SOLUTION/ DROPS
Manufacturer: Guna spa
Category: homeopathic | Type: HUMAN OTC DRUG LABEL
Date: 20221115

ACTIVE INGREDIENTS: INTERLEUKIN-11 4 [hp_C]/30 mL
INACTIVE INGREDIENTS: ALCOHOL 9 mL/30 mL

GUNA- IL 11

ACTIVE INGREDIENTS/PURPOSE

INTERLEUKIN-11 4C Overactive proinflammatory immune activity, Psoriasis and Skin inflammation symptoms

USES

USES: Overactive proinflammatory immune activity, Psoriasis and Skin inflammation symptoms

WARNINGS

Stop use and ask doctor if symptoms worsen or persist more than 5 days

PREGNANCY

If pregnant or breast-feeding ask a doctor before use

WARNINGS

Keep this and all medicines out of reach of children

DIRECTIONS

Take 15 minutes before meals.
Adults and children 12 years and older 20 drops twice a day in a little water. Hold in the mouth for about 30 seconds then swallow.
Children between 12 years and 6 years of age 10 drops twice a day in a little water. Hold in the mouth for about 30 seconds then swallow.
Children under 6 years 5 drops twice a day in a glass of water.

QUESTIONS

Questions?: info@gunainc.com
Tel. (484) 223-3500

Inactive ingredient: Ethyl alcohol 30%.

INDICATIONS AND USAGE

Take 15 minutes before meals.

keep this and all medicines out of children